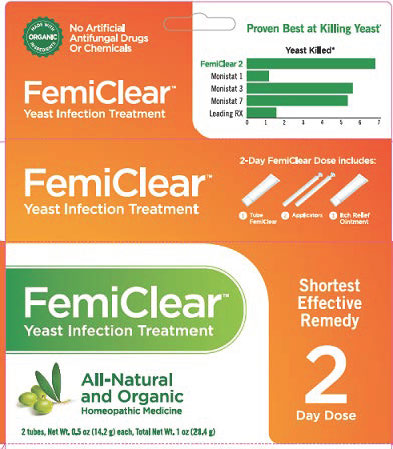 DRUG LABEL: FemiClear

NDC: 71042-007 | Form: KIT | Route: VAGINAL
Manufacturer: Organicare Nature's Science, LLC
Category: homeopathic | Type: HUMAN OTC DRUG LABEL
Date: 20250110

ACTIVE INGREDIENTS: CALENDULA OFFICINALIS FLOWERING TOP 3 [hp_X]/14 g; OLEA EUROPAEA FRUIT VOLATILE OIL 2 [hp_X]/14 g; MELALEUCA CAJUPUTI LEAF OIL 3 [hp_X]/14 g; OLEA EUROPAEA FRUIT VOLATILE OIL 2 [hp_X]/14 g; MELALEUCA CAJUPUTI LEAF OIL 3 [hp_X]/14 g; CALENDULA OFFICINALIS FLOWERING TOP 3 [hp_X]/14 g
INACTIVE INGREDIENTS: LAVENDER OIL; OLIVE OIL; LAVENDER OIL; OLIVE OIL

FEMICLEAR YEAST INFECTION TREATMENT KIT

Drug Facts

Active ingredients

Calendula 3X HPUS

Melaleuca 3X HPUS

Olive Extract 2X HPUS

Purposes

Healing Agent

Anti-Yeast Agent

Antimicrobial and Healing Agent

Uses

See your doctor if this is the first time you have vaginal itching and discomfort to find out if you have a vaginal yeast infection.

- Treats repeat vaginal yeast infections
- To relieve external itching and irritation due to a repeat vaginal yeast infection

Warnings

For vaginal use only.

FemiClear may damage condoms and diaphragms and cause them to fail.

Ask a doctor before use if you

- Have 1 or more of the following: abdominal pain, fever, chills, nausea, vomiting, foul-smelling discharge
- Get vaginal yeast infections often (such as once a month or three in 6 months)
- May have been exposed to the human immunodeficiency virus (HIV) that causes AIDS
- Are under 12 years of age.

When using this product

- Do not have vaginal intercourse
- Do not use tampons, douiches, spermicides, or other vaginal products

Stop use and ask a doctor if

- Symptoms do not improve in 3 days
- Symptoms remain after 7 days
- You get abdominal pain, fever, chills, vomiting, foul-smelling discharge, or hives

PREGNANCY OR BREAST FEEDING

If pregnant or breast-feeding, ask a health professional before use.

Keep out of reach of children. If swallowed, get medical help or contact a Poison Control Center right away.

Directions

- Before use at bedtime, read enclosed instructions for complete directions.
- Adults and children 12 years and older:
- Refrigerate Vaginal Ointment for 20 minutes immediately before use.
- To protect clothes, use panty liner.
- Fill applicator with FemiClear Vaginal Ointment as shown.
- Lie down in bed. Insert applicator into vagina and inject Femiclear. Remain lying down to avoid leakage. Repeat on second night. Discard applicator after each use.
- External Itch Ointment: Squeeze a small amount of ointment onto your fingertip. Apply the ointment onto the itchy, irritated skin outside the vagina. Use as needed.
- Children under 12 years old: ask a doctor

Other information

- Store at 68-77°F (20-25°C)
- if liquified, refrigerate 20 minutes to thicken

Inactive ingredients

oxygenated olive oil, pure essential oil (lavender)

Questions?

Call 512-401-3572 or visit FemiClear.com

Distributed by

OrganiCare®

Austin, TX 78744

Made in Italy

PACKAGE LABEL

No Artificial Antifungal Drugs or Chemicals

FemiClear™

Yeast Infection Treatment

All-Natural and Organic

Homeopathic Medicine

Shortest Effective Remedy

2 Day Dose

1 tubes, Net Wt. 0.5 oz (14.2 g) each, Total Wt. 1 oz (28.4 g)